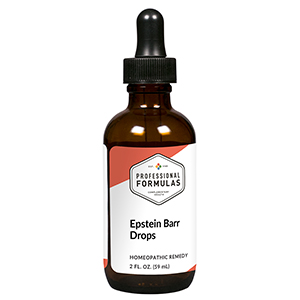 DRUG LABEL: Epstein Barr Drops
NDC: 63083-2021 | Form: LIQUID
Manufacturer: Professional Complementary Health Formulas
Category: homeopathic | Type: HUMAN OTC DRUG LABEL
Date: 20190815

ACTIVE INGREDIENTS: BOS TAURUS BONE MARROW 6 [hp_X]/59 mL; CAUSTICUM 6 [hp_X]/59 mL; PHYTOLACCA AMERICANA ROOT 6 [hp_X]/59 mL; TOXICODENDRON PUBESCENS LEAF 6 [hp_X]/59 mL; BOS TAURUS SPLEEN 6 [hp_X]/59 mL; HYSSOPUS OFFICINALIS WHOLE 6 [hp_X]/59 mL; HUMAN HERPESVIRUS 5 12 [hp_X]/59 mL; HUMAN HERPESVIRUS 4 12 [hp_X]/59 mL; HAEMOPHILUS INFLUENZAE 12 [hp_X]/59 mL; STREPTOCOCCUS VIRIDANS GROUP 12 [hp_X]/59 mL; TOXOPLASMA GONDII 12 [hp_X]/59 mL
INACTIVE INGREDIENTS: ALCOHOL; WATER

C21

ACTIVE INGREDIENTS

Bone marrow 6X, 12X, 30X
Causticum 6X, 12X, 30X
Phytolacca decandra 6X, 12X, 30X
Rhus toxicodendron 6X, 12X, 30X
Spleen 6X, 12X, 30X
Thymus 6X, 12X, 30X
Cytomegalovirus 12X, 30X, 60X, 100X
Epstein-Barr virus 12X, 30X, 60X, 100X
Haemophilus influenzae 12X, 30X, 60X, 100X
Hemolytic streptococcus 12X, 30X, 60X, 100X
Mononucleosis 12X, 30X, 60X, 100X
Toxoplasmosis 12X, 30X, 60X, 100X

QUESTIONS

Professional Formulas

PO Box 2034 Lake Oswego, OR 97035

INDICATIONS

For the temporary relief of fatigue, low-grade fever, sore throat, or weak or sore muscles.*

PURPOSE

*Claims based on traditional homeopathic practice, not accepted medical evidence. Not FDA evaluated.

WARNINGS

Persistent symptoms may be a sign of a serious condition. If symptoms persist or are accompanied by a fever, rash, or persistent headache, consult a doctor. Keep out of the reach of children. In case of overdose, get medical help or contact a poison control center right away. If pregnant or breastfeeding, ask a healthcare professional before use.

Keep out of the reach of children.

PREGNANCY OR BREAST FEEDING

If pregnant or breastfeeding, ask a healthcare professional before use.

DIRECTIONS

Place drops under tongue 30 minutes before/after meals. Adults and children 12 years and over: Take 10 drops up to 3 times per day for up to 6 weeks. For immediate onset of symptoms, take 10 to 15 drops every 15 minutes up to 3 hours. For less severe symptoms, take 10-15 drops hourly up to 8 hours. Consult a physician for use in children under 12 years of age.

OTHER INFORMATION

Tamper resistant. If seal is broken, do not use. After opening, close container tightly and store at room temperature away from heat.

INACTIVE INGREDIENTS

20% ethanol, purified water.

LABEL

Est 1985

Professional Formulas

Complementary Health

Epstein Barr Drops

Homeopathic Remedy

2 FL. OZ. (59 mL)